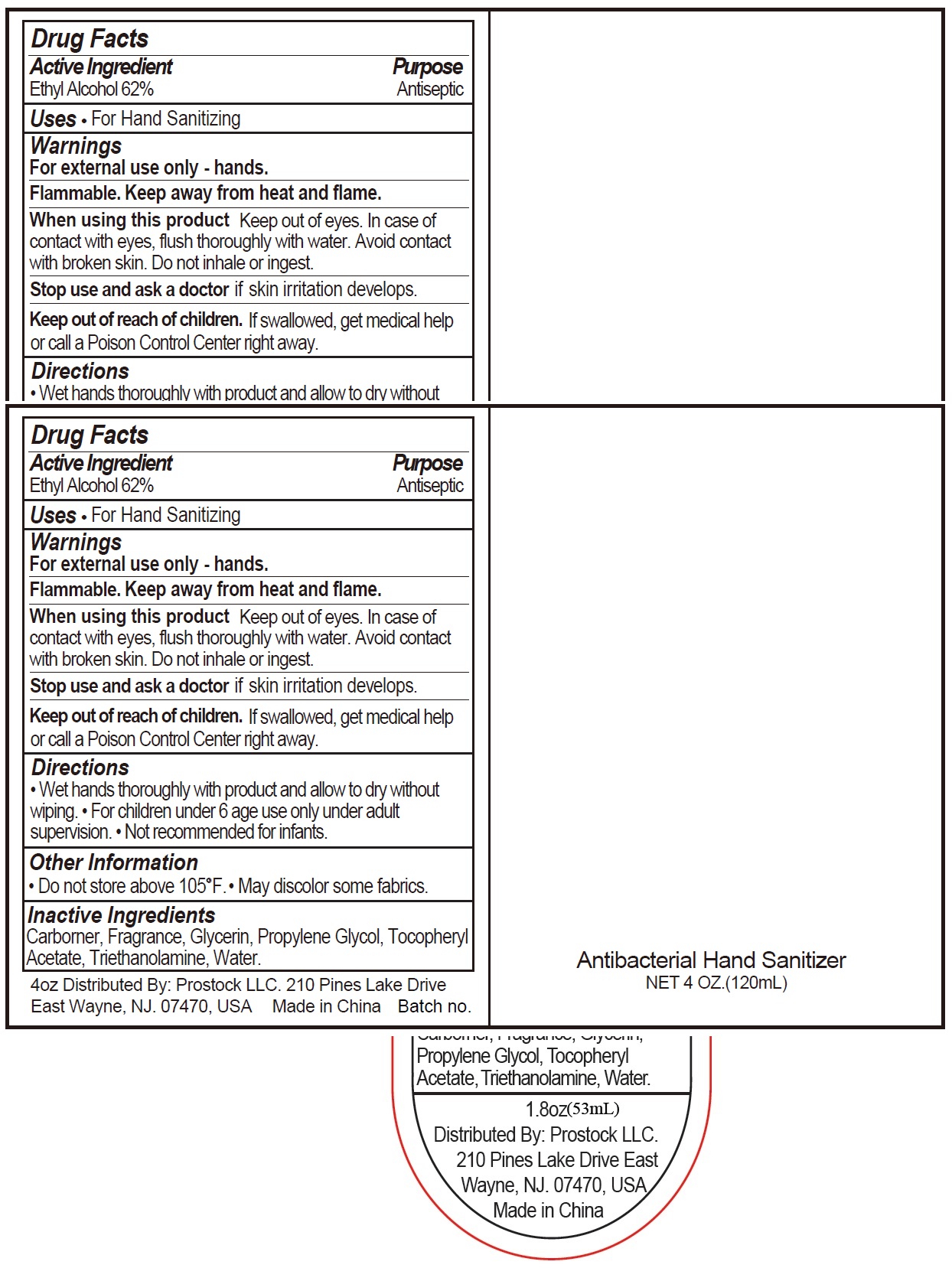 DRUG LABEL: Antibacterial Hand Sanitizer
NDC: 73796-111 | Form: GEL
Manufacturer: Prostock LLC
Category: otc | Type: HUMAN OTC DRUG LABEL
Date: 20231106

ACTIVE INGREDIENTS: ALCOHOL 0.62 mL/1 mL
INACTIVE INGREDIENTS: CARBOMER HOMOPOLYMER, UNSPECIFIED TYPE; GLYCERIN; PROPYLENE GLYCOL; .ALPHA.-TOCOPHEROL ACETATE; TROLAMINE; WATER

Antibacterial Hand Sanitizer

Active Ingredients

Ethyl Alcohol 62%

Purpose

Antiseptic

Uses

For hand washing to decrease bacteria on the skin.

Warnings

For external use only.

Flammable. Keep away from heat and flame.

When using this product

Keep out of eyes. In case of contact with eyes, flush thoroughly with water. Avoid contact with broken skin. Do not inhale or ingest.

Stop use and ask a doctor if

if skin irritation develops.

Keep out of reach of children.

If swallowed, get medical help or call a Poison Control Center right away.

Directions

Wet hands thoroughly with a product and allow to dry without wiping.

Other Information

Store under 105 F. o

Inactive Ingredients

Water, Polyquaternium-10, Propylene Glycol, Glycerin, Polyaminopropyl Biguanide, PEG-40 Hydrogenated Castor Oil, Fragrance, Tromethamine